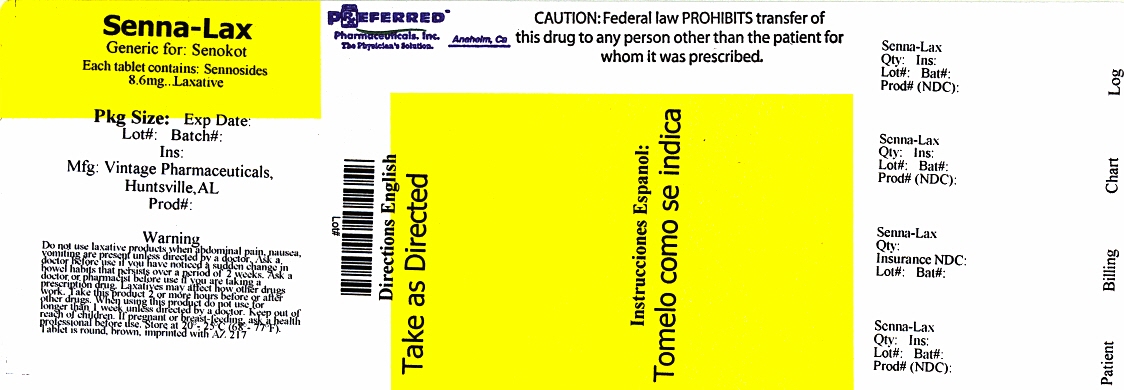 DRUG LABEL: Senna-Lax
NDC: 68788-9685 | Form: TABLET
Manufacturer: Preferred Pharmaceuticals, Inc.
Category: otc | Type: HUMAN OTC DRUG LABEL
Date: 20161004

ACTIVE INGREDIENTS: SENNOSIDES A AND B 8.6 mg/1 1
INACTIVE INGREDIENTS: SILICON DIOXIDE; CROSCARMELLOSE SODIUM; DIBASIC CALCIUM PHOSPHATE DIHYDRATE; LACTOSE, UNSPECIFIED FORM; MAGNESIUM STEARATE; CELLULOSE, MICROCRYSTALLINE; TARTARIC ACID

Senna-Lax

ACTIVE INGREDIENTS (IN EACH TABLET)

Sennosides 8.6 mg

PURPOSE

Laxative

USES

- for relief of occasional constipation and irregularity
- this product produces a bowel movement in 6 to 12 hours

WARNINGS

Do not use

laxative products when abdominal pain, nausea, or vomiting are present unless directed by a doctor

Ask a doctor before use if you have

noticed a sudden change in bowel habits that persists over a period of 2 weeks

Ask a doctor or pharmacist if you are

taking a prescription drug. Laxatives may affect how other drugs work. Take this product 2 or more hours before or after other drugs.

When using this product

do not use for longer than 1 week unless directed by a doctor

Stop use and ask a doctor

rectal bleeding or failure to have a bowel movement occur after use of a laxative. These could be signs of a serious condition.

If pregnant or breast-feeding

ask a health professional before use.

Keep Out of Reach of Children.

In case of overdose, get medical help or contact a Poison Control Center right away.

DIRECTIONS

- Take preferably at bedtime or as directed by doctor
- If you do not have a comfortable bowel movement by the second day, increase dose by 1 tablet (do not exceed maximum dosage) or decrease dose until you are comfortable

Age | Starting dosage | Maximum dosage
Adults and children over 12 years | 2 tablets once a day | 4 tablets twice a day
children 6 to under 12 years | 1 tablet once a day | 2 tablets twice a day
children 2 to under 6 years | 1/2 tablet once a day | 1 tablet twice a day
children under 2 years | consult a doctor

OTHER INFORMATION

- each tablet contains: calcium 50 mg
- store at 20°-25°C (68°-77°F)

You may report serious side effects to: 1-888-952-0050.

INACTIVE INGREDIENTS

colloidal silicon dioxide, croscarmellose sodium, dibasic calcium phosphate, magnesium stearate, microcrystalline cellulose

PRINCIPAL DISPLAY PANEL

Senna Lax

Repackaged By: Preferred Pharmaceuticals Inc.